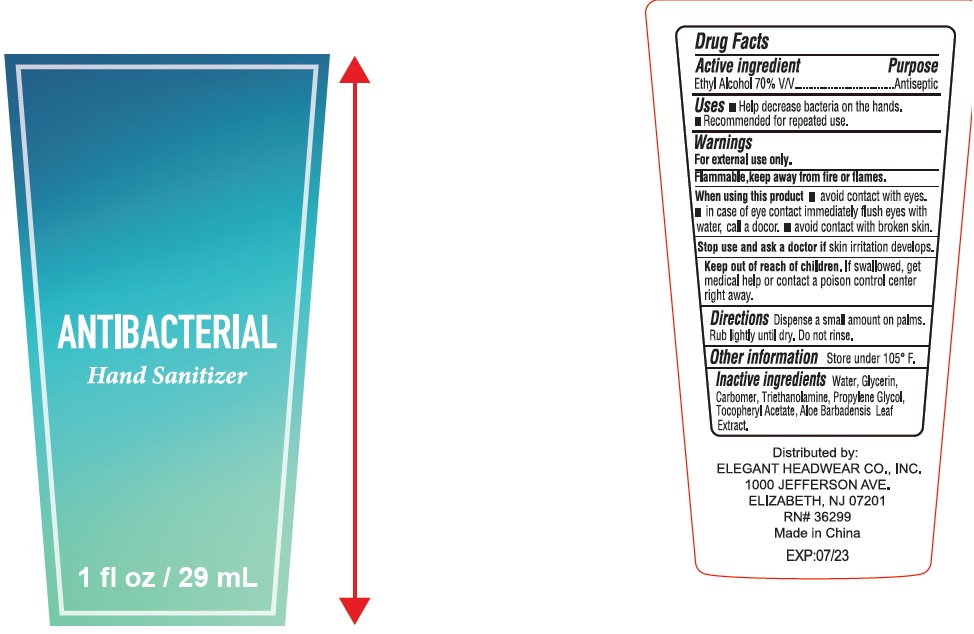 DRUG LABEL: Antibacterial Hand Sanitizer
NDC: 74149-046 | Form: GEL
Manufacturer: Yiwu Yangjie Daily Chemicals Co.,Ltd.
Category: otc | Type: HUMAN OTC DRUG LABEL
Date: 20201116

ACTIVE INGREDIENTS: alcohol 70 mL/100 mL
INACTIVE INGREDIENTS: WATER; PROPYLENE GLYCOL; ALOE VERA LEAF; GLYCERIN; .ALPHA.-TOCOPHEROL ACETATE; TROLAMINE

Drug facts

Active ingredient Ethyl Alcohol ........... 70% W/W

PURPOSE

Antiseptic

KEEP OUT OF REACH OF CHILDREN

If swallowed, get medical help or contact a poison control center right away.

INDICATIONS AND USAGE

- Hand sanitizer to help decrease bacteria on the skin.
- recommended for repeated use

WARNINGS

For external use only - hands
Flammable. Keep away from heat or flame.

When using this product avoid contact with eyes and nose. In case of contact flush eyes with water.

Stop use and ask a doctor If irritation or redness develops.

DOSAGE AND ADMINISTRATION

wet hands thoroughly with product and allow to dry.

INACTIVE INGREDIENT

Water, Glycerin, Carbomer, Triethanolamine, Propylene Glycol, Tocopheryl Acetate, Aloe Barbadensis Leaf Extract